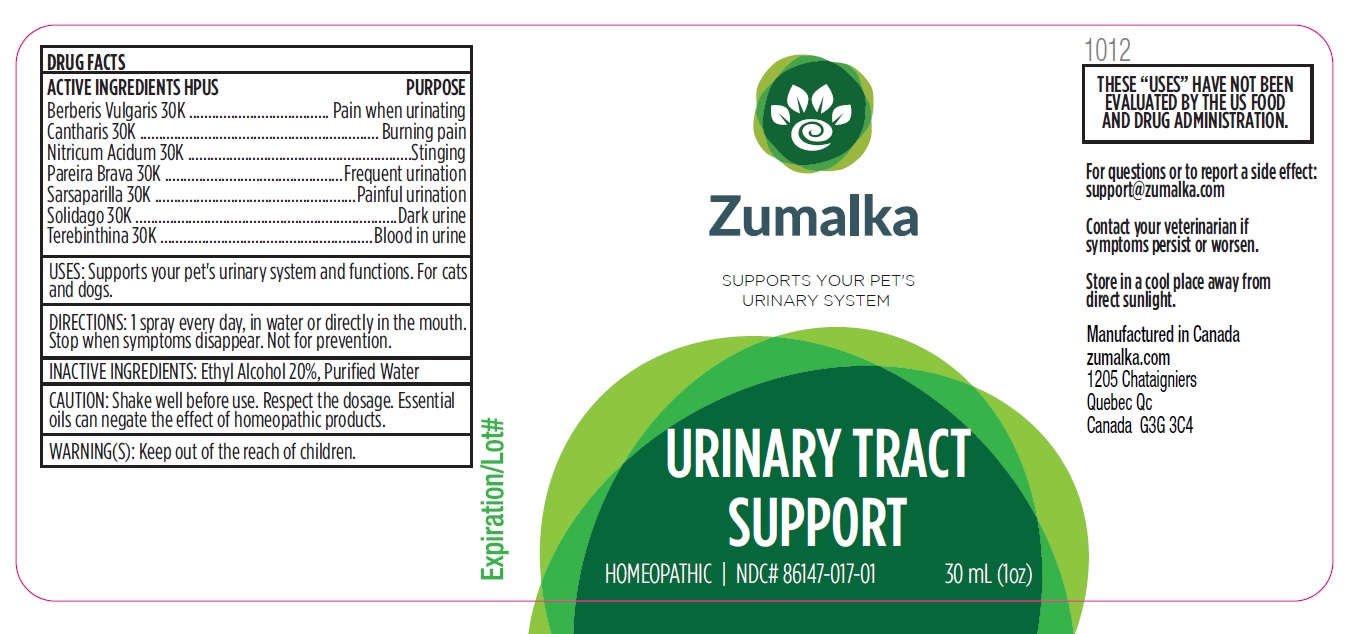 DRUG LABEL: URINARY TRACT SUPPORT
NDC: 86147-017 | Form: LIQUID
Manufacturer: Groupe Cyrenne Inc.
Category: homeopathic | Type: OTC ANIMAL DRUG LABEL
Date: 20251120

ACTIVE INGREDIENTS: BERBERIS VULGARIS ROOT BARK 30 [kp_C]/30 mL; LYTTA VESICATORIA 30 [kp_C]/30 mL; SOLIDAGO VIRGAUREA FLOWERING TOP 30 [kp_C]/30 mL; NITRIC ACID 30 [kp_C]/30 mL; CHONDRODENDRON TOMENTOSUM ROOT 30 [kp_C]/30 mL; SMILAX ORNATA ROOT 30 [kp_C]/30 mL; TURPENTINE OIL 30 [kp_C]/30 mL
INACTIVE INGREDIENTS: WATER; ALCOHOL

Active ingredient

Berberis Vulgaris 30k, Cantharis 30k, Nitricum Acidum 30k, Pareira Brava 30k, Sarsaparilla 30k, Solidago 30k, Terebinthina 30k

Active ingredient Purpose

Berberis Vulgaris 30K Pain when urinating

Cantharis 30K Burning pain

Nitricum Acidum 30K Stinging

Pareira Brava 30K Frequent urination

Sarsaparilla 30K Painful urination

Solidago 30K Dark urine

Terebinthina 30K Blood in urine

Uses

Supports your pet's urinary system and functions. For cats and dogs only.

Cautions

Shake well before use. Respect the dosage. Essential oils can negate the effects of homeopathic products. Store in a cool place away from direct sunlight.

Warnings

Keep out of the reach of children.

Direction

1 spray every day, in water or directly in the mouth. Stop when symptoms disappear. Not for prevention.

Inactive ingredient

Ethyl alcohol 20%, purified water

Other information

The letters "HPUS" indicate that the active ingredients are in the official Homeopathic Pharmacopoeia of the United States. Homeopathic remedy. Store at room temperature.